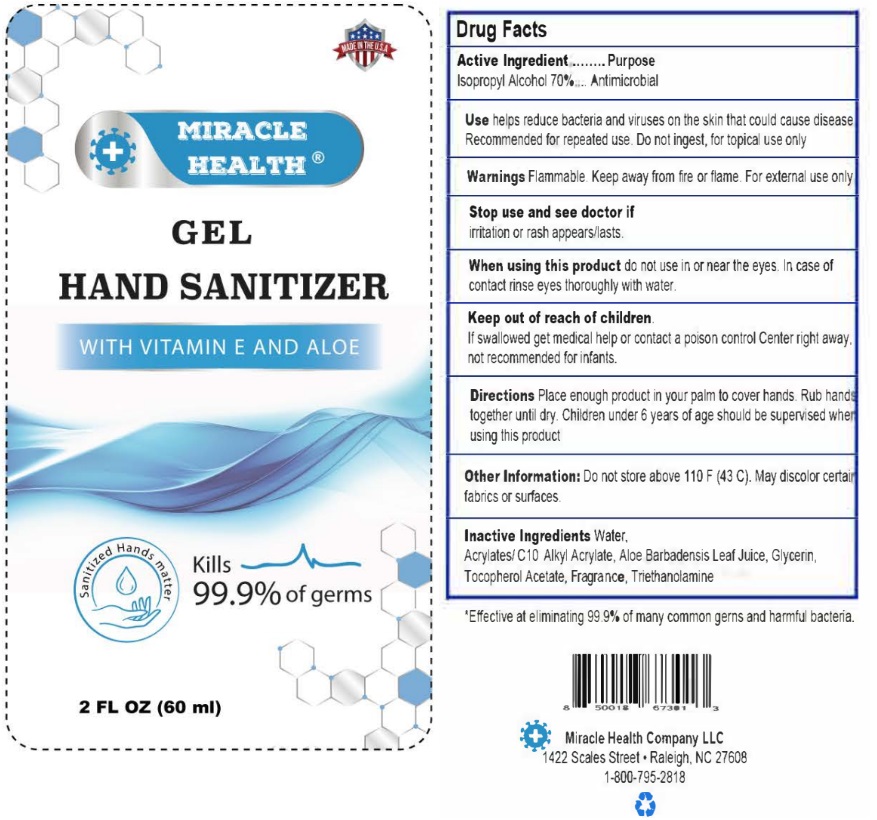 DRUG LABEL: Miracle Health Gel Hand Sanitizer
NDC: 90090-001 | Form: GEL
Manufacturer: CORONET CERAMICS, INC.
Category: otc | Type: HUMAN OTC DRUG LABEL
Date: 20200804

ACTIVE INGREDIENTS: ISOPROPYL ALCOHOL 70 mL/100 mL
INACTIVE INGREDIENTS: WATER; CARBOMER HOMOPOLYMER, UNSPECIFIED TYPE; ALOE VERA LEAF; GLYCERIN; .ALPHA.-TOCOPHEROL ACETATE; FRAGRANCE LAVENDER & CHIA F-153480; TROLAMINE

Active Ingredient

Isopropyl Alcohol 70% v/v.

Purpose

Antimicrobial

Use

- Helps reduce bacteria and viruses on the skin that could cause disease.
- Recommended for repeated use.
- Do not ingest, for topical use only.

Warnings

Flammable. Keep away from fire or flame. For external use only.

Do not use

- in children less than 2 months of age
- on open skin wounds

Keep out of reach of children. If swallowed, get medical help or contact a Poison Control Center right away.

Directions

- Place enough product in your palm to cover hands. Rub hands togethe until dry.
- Children under 6 years of age should be supervised when using this product.

Other Information

- Do not store above 110 F (43 C).
- May discolor certain fabrics or surfaces.

Inactive ingredients

Water, Acrylates/C10 Alkyl Arcylate, Aloe Barlladensis Leaf Juice. Glycerin, Tocopherol Acetate, Fragrance, Triethanolamine